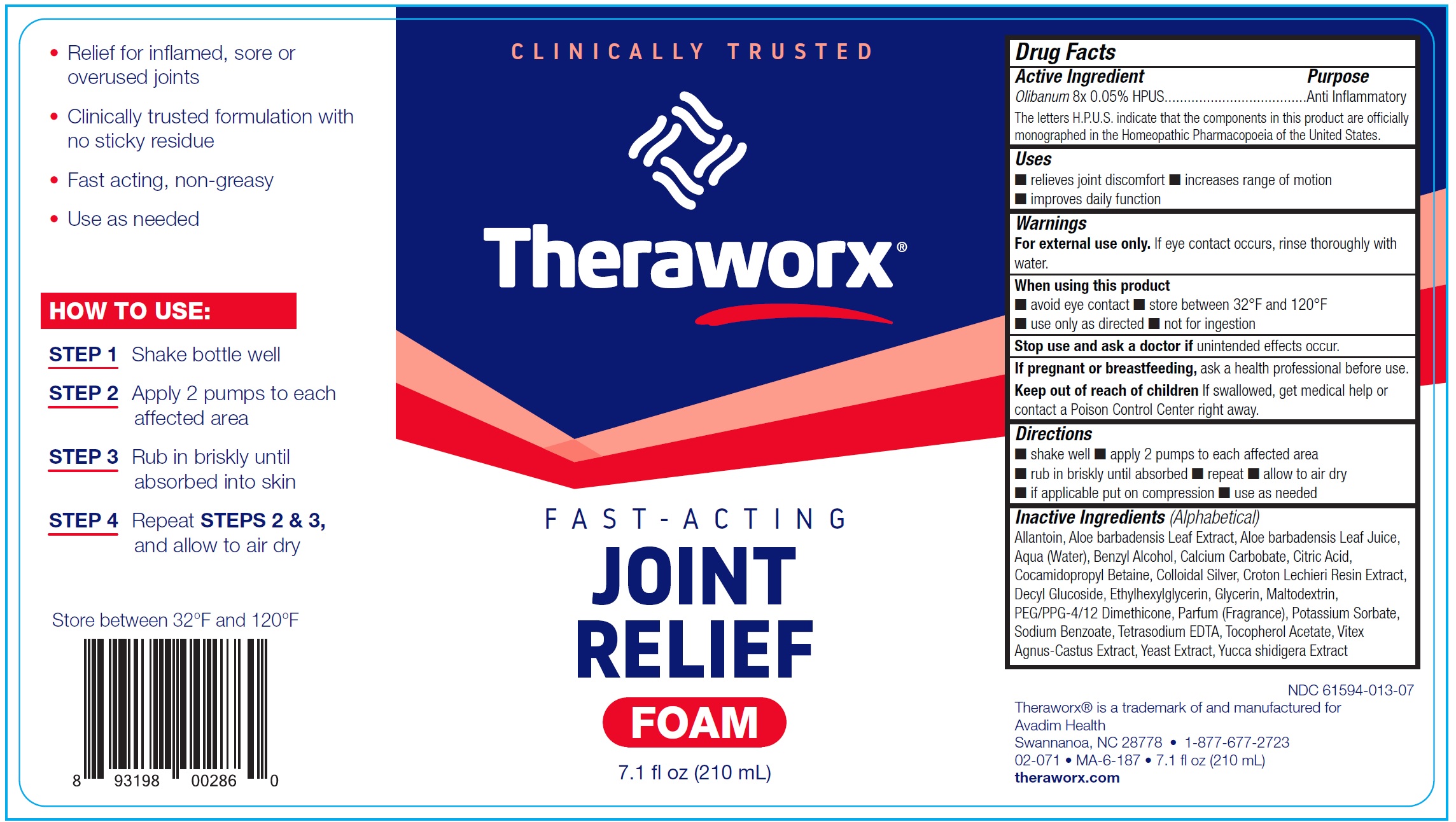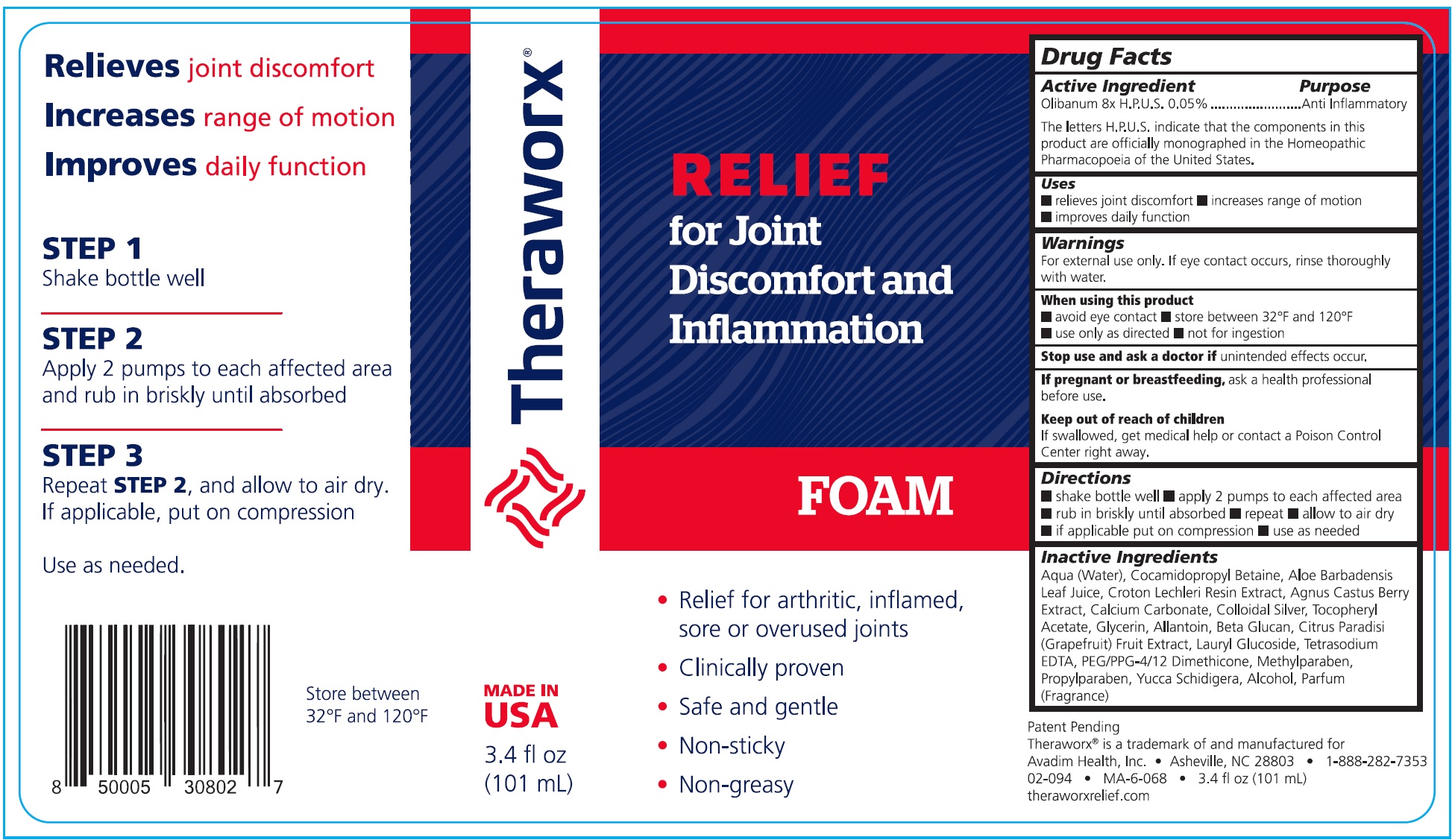 DRUG LABEL: Theraworx Relief Joint Discomfort and Inflammation
NDC: 61594-013 | Form: LIQUID
Manufacturer: AVADIM HOLDINGS, INC.
Category: homeopathic | Type: HUMAN OTC DRUG LABEL
Date: 20240618

ACTIVE INGREDIENTS: FRANKINCENSE 8 [hp_X]/210 mL
INACTIVE INGREDIENTS: WATER; COCAMIDOPROPYL BETAINE; ALOE VERA LEAF; CROTON LECHLERI RESIN; CALCIUM CARBONATE; SILVER; .ALPHA.-TOCOPHEROL ACETATE; GLYCERIN; ALLANTOIN; GRAPEFRUIT; LAURYL GLUCOSIDE; EDETATE SODIUM; PEG/PPG-4/12 DIMETHICONE; METHYLPARABEN; PROPYLPARABEN; YUCCA SCHIDIGERA WHOLE; ALCOHOL

Theraworx Relief Joint Discomfort and Inflammation

Active Ingredient

Olibanum 8x H.P.U.S. 0.05

The letters H.P.U.S. indicates that the components in this product are officially monographed in the Homeopathic Pharmacopoeia of the United States.

Purpose

Anti Inflammatory

Uses

- relives joint discomfort
- increases range of motion
- improves daily function

Warnings

For external use only. If eye contact occurs, rinse thoroughly with water.

When using this product

- avoid eye contact
- store between 32°F and 120°F
- use only as directed
- not for ingestion

Stop use and ask a doctor if

unintended effects occur.

If pregnant or breastfeeding,

ask a health professional before use.

Keep out of reach of children

If swallowed, get medical help or contact a Poison Control Center right away.

Directions

- shake bottle well
- apply 2 pumps to each affected area
- rub in briskly until absorbed
- repeat
- allow to air dry
- if applicable put on compression
- use as needed

Inactive Ingredients

Aqua (Water), Cocamidopropyl Betaine, Aloe Barbadensis Leaf Juice, Croton Lechleri Resin Extract, Agnus Castus Berry Extract, Calcium Carbonate, Colloidal Silver, Tocopheryl Acetate, Glycerin, Allantoin, Beta Glucan, Citrus Paradisi (Grapefruit) Fruit Extract, Lauryl Glucoside, Tetrasodium EDTA, PEG/PPG-4/12 Dimethicone, Methylparaben, propylparaben, Yucca Schidigera, Alcohol, Parfum (Fragrance)